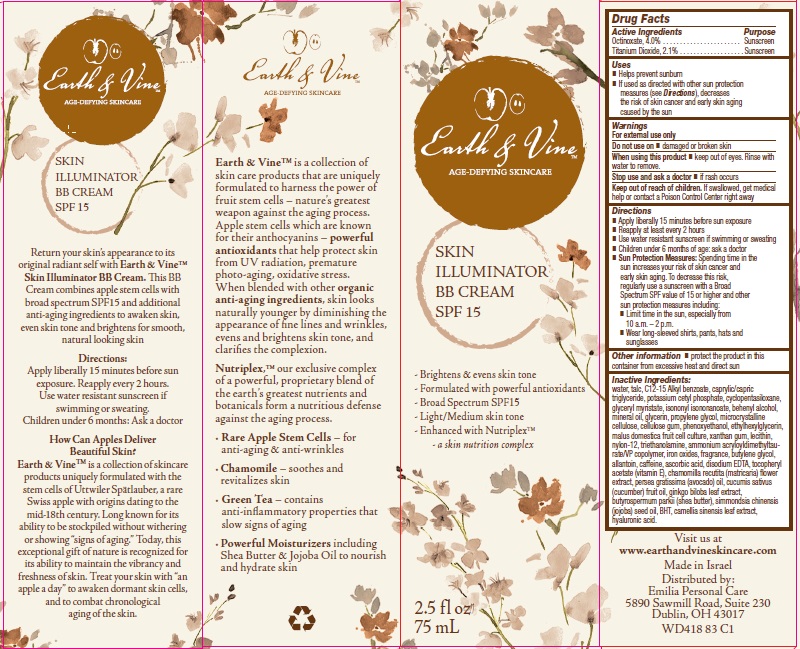 DRUG LABEL: Earth and Vine BB Broad Spectrum SPF 15 Sunscreen
NDC: 42421-419 | Form: CREAM
Manufacturer: Emilia Personal Care Inc.
Category: otc | Type: HUMAN OTC DRUG LABEL
Date: 20141002

ACTIVE INGREDIENTS: OCTINOXATE 4 g/100 g; TITANIUM DIOXIDE 2.1 g/100 g
INACTIVE INGREDIENTS: WATER; TALC; ALKYL (C12-15) BENZOATE; MEDIUM-CHAIN TRIGLYCERIDES; POTASSIUM CETYL PHOSPHATE; CYCLOMETHICONE 5; GLYCERYL MYRISTATE; ISONONYL ISONONANOATE; DOCOSANOL; MINERAL OIL; GLYCERIN; PROPYLENE GLYCOL; CELLULOSE, MICROCRYSTALLINE; CARBOXYMETHYLCELLULOSE SODIUM; PHENOXYETHANOL; ETHYLHEXYLGLYCERIN; APPLE; XANTHAN GUM; NYLON-12; TROLAMINE; AMMONIUM ACRYLOYLDIMETHYLTAURATE/VP COPOLYMER; FERRIC OXIDE RED; BUTYLENE GLYCOL; ALLANTOIN; CAFFEINE; ASCORBIC ACID; EDETATE DISODIUM; .ALPHA.-TOCOPHEROL ACETATE; CHAMOMILE; AVOCADO OIL; CUCUMBER FRUIT OIL; GINKGO; SHEA BUTTER; JOJOBA OIL; BUTYLATED HYDROXYTOLUENE; GREEN TEA LEAF; HYALURONIC ACID

Earth and Vine™ BB Broad Spectrum SPF 15 Sunscreen

Active ingredient

Octinoxate, 4.0%

Titanium Dioxide, 2.1%

Purpose

Sunscreen

Uses

- Helps prevent sunburn
- If used as directed with other sun protection measures (see Directions), decreases the risk of skin cancer and early skin aging caused by the sun

Warnings

For external use only

Do not use on

- damaged or broken skin

When using this product

- keep out of eyes. Rinse with water to remove.

Stop use and ask a doctor

- if rash occurs

Keep Out of Reach of Children.

If swallowed, get medical help or contact a Poison Control Center right away

Directions

- Apply liberally 15 minutes before sun exposure
- Reapply at least every 2 hours
- Use water resistant sunscreen if swimming or sweating
- Children under 6 months of age: ask a doctor
- Sun Protection Measures: Spending time in the sun increases your risk of skin cancer and early skin aging. To decrease this risk, regularly use a sunscreen with a Broad Spectrum SPF value of 15 or higher and other sun protection measures including:
  1. Limit time in the sun, especially from 10 a.m. – 2 p.m.
  2. Wear long-sleeved shirts, pants, hats and sunglasses

Other Information

- protect the product in this container from excessive heat and direct sun

Inactive ingredients

water, talc, C12-15 Alkyl benzoate, caprylic/capric triglyceride, potassium cetyl phosphate, cyclopentasiloxane, glyceryl myristate, isononyl isononanoate, behenyl alcohol, mineral oil, glycerin, propylene glycol, microcrystalline cellulose, cellulose gum, phenoxyethanol, ethylhexylglycerin, malus domestica fruit cell culture, xanthan gum, lecithin, nylon-12, triethanolamine, ammonium acryloyldimethyltaurate/VP copolymer, iron oxides, fragrance, butylene glycol, allantoin, caffeine, ascorbic acid, disodium EDTA, tocopheryl acetate (vitamin E), chamomilla recutita (matricaria) flower extract, persea gratissima (avocado) oil, cucumis sativus (cucumber) fruit oil, ginkgo biloba leaf extract, butyrospermum parkii (shea butter), simmondsia chinensis (jojoba) seed oil, BHT, camellia sinensis leaf extract, hyaluronic acid.

Package/Label Principal Display Panel

Earth & Vine™
AGE-DEFYING SKINCARE

SKIN
ILLUMINATOR
BB CREAM
SPF 15

- Brightens & evens skin tone
- Formulated with powerful antioxidants
- Broad Spectrum SPF15
- Light/Medium skin tone
- Enhanced with Nutriplex™
  - a skin nutrition complex

2.5 fl oz
75 mL

Return your skin’s appearance to its original radiant self with Earth & Vine™ Skin Illuminator BB Cream. This BB Cream combines apple stem cells with broad spectrum SPF15 and additional anti-aging ingredients to awaken skin, even skin tone and brightens for smooth, natural looking skin

Directions:
Apply liberally 15 minutes before sun exposure. Reapply every 2 hours. Use water resistant sunscreen if swimming or sweating.
Children under 6 months: Ask a doctor

How Can Apples Deliver Beautiful Skin?

Earth & Vine™ is a collection of skincare products uniquely formulated with the stem cells of Uttwiler Spätlauber, a rare Swiss apple with origins dating to the mid-18th century. Long known for its ability to be stockpiled without withering or showing “signs of aging.” Today, this exceptional gift of nature is recognized for its ability to maintain the vibrancy and freshness of skin. Treat your skin with “an apple a day” to awaken dormant skin cells, and to combat chronological aging of the skin.

Earth & Vine™ is a collection of skin care products that are uniquely formulated to harness the power of fruit stem cells – nature’s greatest weapon against the aging process. Apple stem cells which are known for their anthocyanins – powerful antioxidants that help protect skin from UV radiation, premature photo-aging, oxidative stress. When blended with other organic anti-aging ingredients, skin looks naturally younger by diminishing the appearance of fine lines and wrinkles, evens and brightens skin tone, and clarifies the complexion.

Nutriplex,™ our exclusive complex of a powerful, proprietary blend of the earth’s greatest nutrients and botanicals form a nutritious defense against the aging process.

- Rare Apple Stem Cells – for anti-aging & anti-wrinkles
- Chamomile – soothes and revitalizes skin
- Green Tea – contains anti-inflammatory properties that slow signs of aging
- Powerful Moisturizers including Shea Butter & Jojoba Oil to nourish and hydrate skin

Visit us at
www.earthandvineskincare.com

Made in Israel
Distributed by:
Emilia Personal Care
5890 Sawmill Road, Suite 230
Dublin, OH 43017

WD418 83 C1

Carton Label